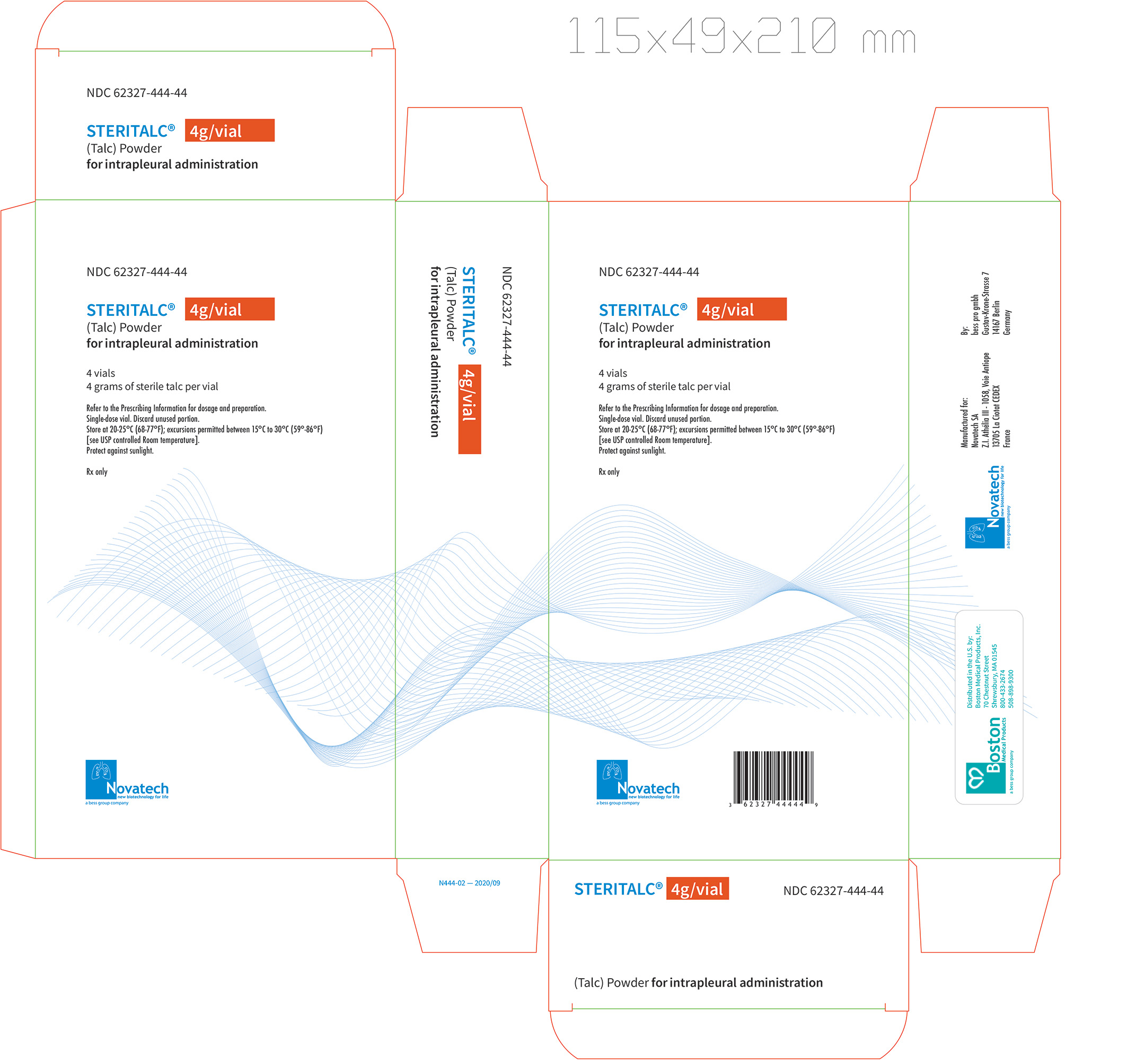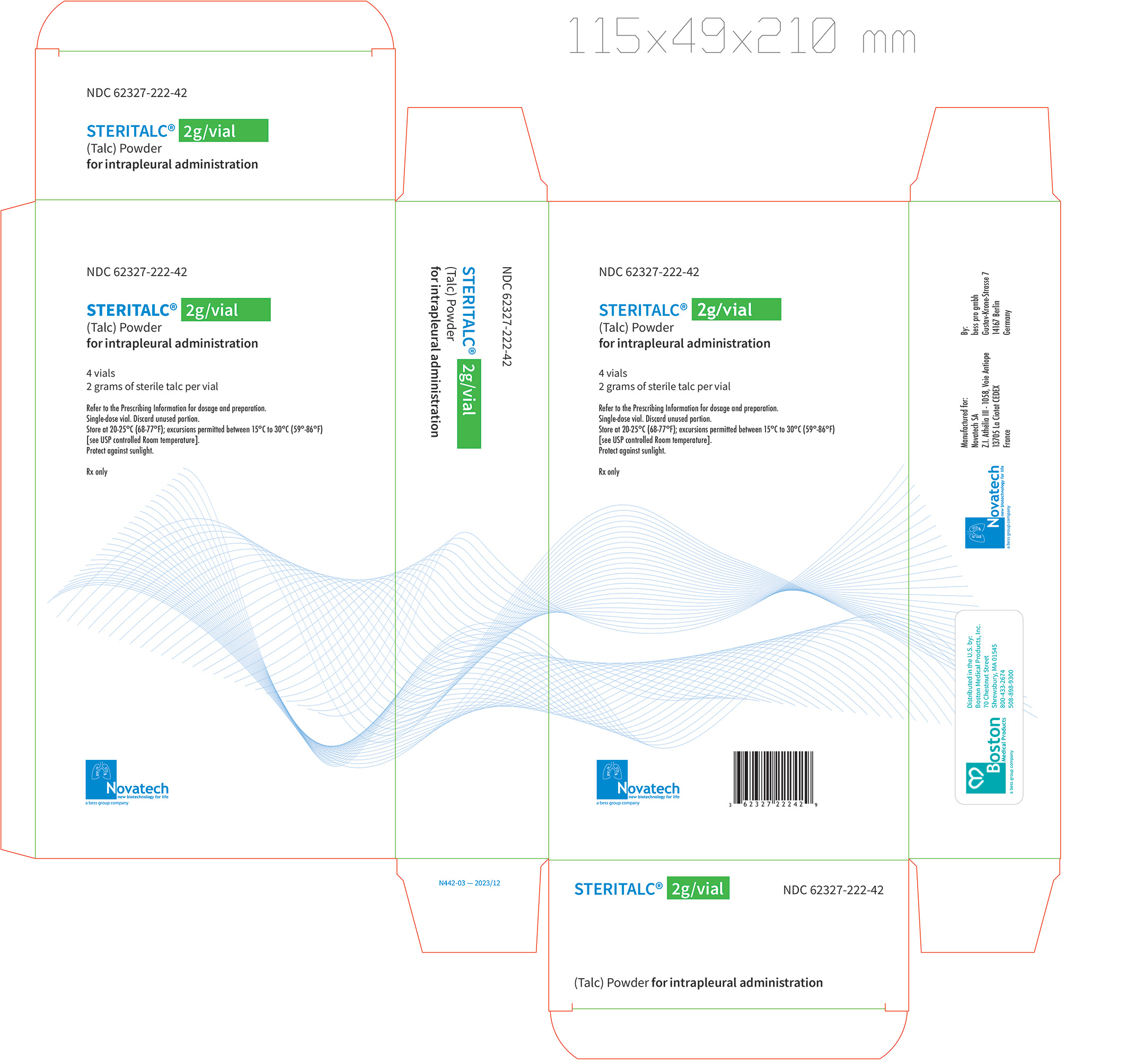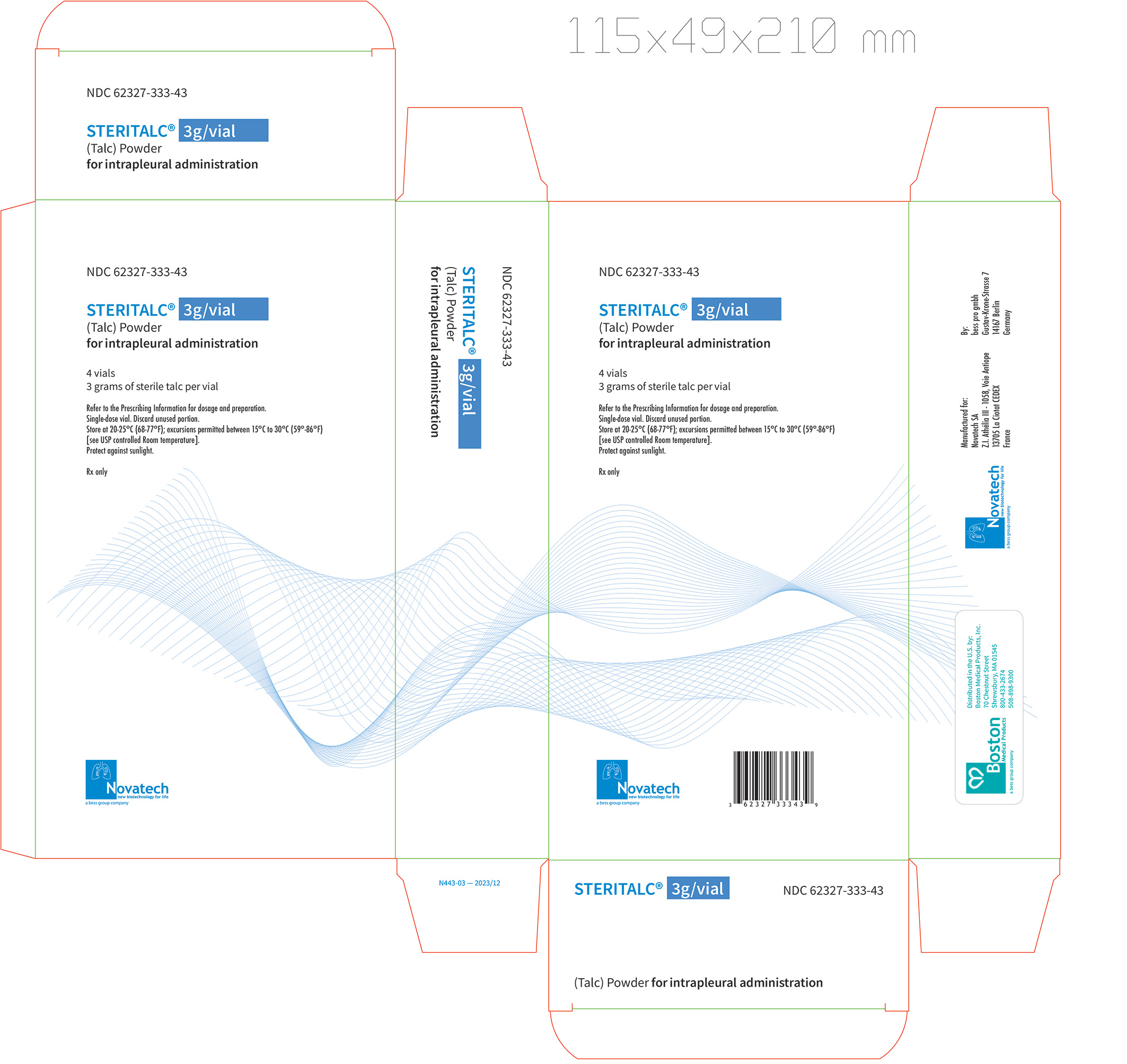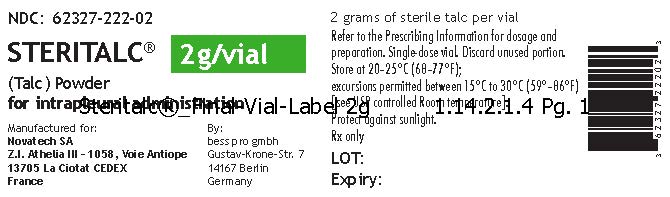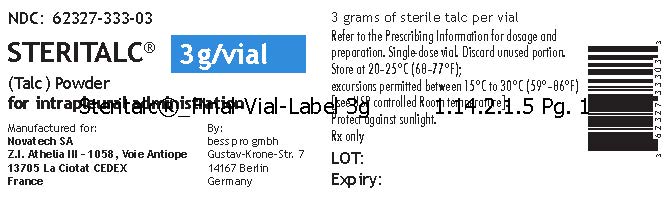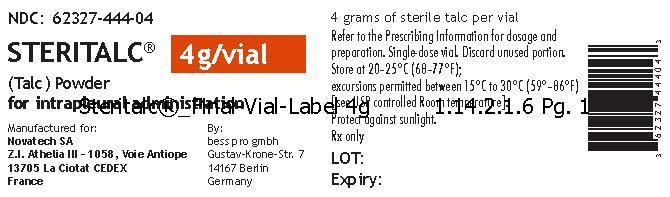 DRUG LABEL: Steritalc
NDC: 62327-444 | Form: POWDER
Manufacturer: Novatech SA
Category: prescription | Type: HUMAN PRESCRIPTION DRUG LABEL
Date: 20250625

ACTIVE INGREDIENTS: TALC 4 g/50 mL

HIGHLIGHTS OF PRESCRIBING INFORMATION

These highlights do not include all the information needed to use STERITALC® safely and effectively. See full prescribing information for STERITALC®.
STERITALC® (talc), powder, for intrapleural use
Initial U.S. Approval: 2003

1.INDICATIONS AND USAGE

___________ INDICATIONS AND USAGE____________
STERITALC® is a sclerosing agent indicated:

- To decrease the recurrence of malignant pleural effusions in symptomatic patients following maximal drainage of the pleural effusion. (1.1)
- In adults to decrease the recurrence of pneumothorax. (1.2)

2. DOSAGE AND ADMINISTRATION

________ DOSAGE AND ADMINISTRATION________

- Malignant Pleural Effusion: The recommended dose is 2 to 5 grams administered intrapleurally. (2.2)
- Pneumothorax: The recommended dose is 2 grams administered intrapleurally.
- Do not exceed a total cumulative dosage of 10 grams per procedure. (2.3)
- Prepare and administer as recommended. (2.5)

3. DOSAGE FORMS AND STRENGTHS

_______ DOSAGE FORMS AND STRENGTHS_______

- Powder: 2 grams, in a 50 mL single-dose vial (3)
- Powder: 4 grams, in a 50 mL single-dose vial (3)
- Powder: 3 grams, in a 10 mL single-dose vial (3)

4. CONTRAINDICATIONS

_____________ CONTRAINDICATIONS_____________

Pregnancy. (4, 5.3, 8.1)

5. WARNINGS AND PRECAUTIONS

_ ______WARNINGS AND PRECAUTIONS_____________

- Pneumonitis and Acute Respiratory Distress Syndrome (ARDS): Acute Pneumonitis and ARDS, have been reported with intrapleural use of various talc products. (5.1)
- Interference with Future Procedures: Sclerosis of the pleural space may preclude or complicate subsequent ipsilateral surgery and diagnostic procedures. (5.2)
- Lead Content: STERITALC® contains lead as an impurity. May cause lead toxicity, especially in children. (5.3)
- Asbestos Content: Talc products may contain trace amounts of asbestos. Exposure to asbestos may increase the risk of mesotheliomas and other cancers. (5.4, 11)

RECENT MAJOR CHANGES

Warnings and Precautions (5.4) 06/2025

6. ADVERSE REACTIONS

_____________ ADVERSE REACTIONS_____________

Common adverse reactions are fever and pain. (6)

To report suspected adverse reactions contact Boston Medical Product Inc., at 508-898-9300 and FDA at 1-800-332-1088 or www.fda.gov/medwatch.

8. USE IN SPECIFIC POPULATIONS

------------USE IN SPECIFIC POPULATIONS--------------

- Females and Males of Reproductive Potential: Advise females of reproductive potential to use effective contraception. (8.3)
- Lactation: Advise women not to breastfeed. (8.2)

FULL PRESCRIBING INFORMATION

1.INDICATIONS AND USAGE

1.1 Malignant Pleural Effusion

STERITALC is indicated to decrease the recurrence of malignant pleural effusions in symptomatic patients following maximal drainage of the pleural effusion.

1.2 Pneumothorax

STERITALC is indicated in adults to decrease the recurrence of pneumothorax.

2. DOSAGE AND ADMINISTRATION

2.1 Important Use Information

STERITALC is for pleurodesis only - Do NOT administer STERITALC intravenously.

Administer STERITALC after adequate drainage of the pleural effusion or air.

2.2 Recommended Dose for Malignant Pleural Effusion

The recommended dose for malignant pleural effusion is 2 to 5 grams administered intrapleurally. According to the physician’s discretion, and in consideration of diagnosis and patient’s condition, different dosages may be applied, but a total dosage of 10 grams should not be exceeded.

2.3 Recommended Dose for Pneumothorax

The recommended dose for pneumothorax is 2 grams administered intrapleurally. According to physician’s discretion and in consideration of diagnosis and patient’s condition, different dosages may be applied, but a cumulative dosage of 10 grams should not be exceeded.

2.4 Preparation

Slurry for Tube Thoracostomy

STERITALC 2 grams and 4 grams dosage forms

Do not prepare the slurry in advance. Use the slurry immediately after preparation.

Prepare the talc suspension using aseptic technique in an appropriate laminar flow hood as follows:

Step 1: Fully bend or remove the flap into the direction of the arrow. The top can now be punctured to mix the slurry.

Step 2: Using a 16 gauge needle attached to a 60-mL Luer Lok syringe, draw up 50 mL of 0.9 % Sodium Chloride injection, USP. Vent the talc bottle using a needle. Slowly inject the 50 mL of 0.9% Sodium Chloride Injection, USP into the glass vial.

Step 3: Swirl the glass vial to disperse the talc powder.

Step 4: Divide the contents of the glass vial equally into two 60-mL Luer Lok syringes, each attached with a 16 gauge needle, by withdrawing 25 mL of the suspension into each syringe with continuous swirling. Add 0.9% Sodium Chloride Injection, USP to a total volume of 50 mL in each syringe. Draw 10 mL of air into each syringe to the 60 mL mark to serve as a headspace for mixing prior to administration.

For STERITALC 2 grams, each syringe should contain 1 gram of Sterile Talc Powder in 50 mL of 0.9% Sodium Chloride Injection, USP with an air headspace of 10 mL.

For STERITALC 4 grams, each syringe should contain 2 grams of Sterile Talc Powder in 50 mL of 0.9% Sodium Chloride Injection, USP with an air headspace of 10 mL.

Step 5: Label the syringes with the talc concentration, the expiration date and time, the identity of the patient intended to receive the material, and the following statements:

“SHAKE SYRINGE WELL to resuspend before administration”

“FOR PLEURODESIS ONLY – not for intravenous administration”

Step 6: If not used immediately, store prepared suspension in refrigerator. Discard the prepared suspension if not used within 12 hours.

Insufflation/Poudrage

STERITALC 2 grams and 4 grams dosage forms

Use an FDA-approved or cleared device for STERITALC insufflation/poudrage.

Step 1: Fully remove the top from the vial.

Step 2: Fill the content into the applicator for insufflation/poudrage.

Step 3: Follow the selected device manufacturer's instructions for insufflation/poudrage.

STERITALC 3 grams dosage form

STERITALC 3 grams is designed to be used for the administration of talc in combination with a compatible FDA approved or FDA cleared device intended for manual insufflation of medical grade talc into the pleural cavity during pleurodesis such as Novatech SA’s NOVATECH® TALCAIR™.

Step 1: Remove the aluminum tear-off cap from the vial.

Step 2: Remove the stopper from the vial.

Step 3: Close the vial with the vial coupling.

Step 4: Firmly press the vial coupling onto the vial until you feel and hear the lid "click" onto the vial top. To do this, place the vial on a firm and level base.

Step 5: Connect the insufflation bulb to the vial coupling using the Luer lock connector.

Step 6: Ensure that all components are firmly connected with each other.

2.5 Administration

Slurry for Tube Thoracostomy

STERITALC 2 grams and 4 grams dosage forms

Prior to administration, continuously agitate the syringes to evenly redisperse the talc and avoid settlement. Immediately prior to administration, vent the 10 mL air headspace from each syringe. Administer the talc suspension through the chest tube according to standard procedures.

Step 1: Inject the slurry through the pleural drainage into the pleural cavity.

Step 2: Clamp the pleural drainage. Keep the negative pressure in the pleural cavity.

Step 3: While the slurry remains in the pleural cavity, reposition the patient regularly to achieve even distribution of the slurry.

Step 4: Aspirate the slurry through the pleural drainage.

Insufflation/Poudrage

Perform intervention by means of a tube thoracoscopy. Follow the selected device manufacturer's instructions for insufflation/poudrage.

STERITALC 2 grams and 4 grams dosage forms

Step 1: Introduce the cannula into the trocar.

Step 2: Distribute the talc evenly in the pleural cavity. To do this, carefully spray several times. After spraying a few times, change the cannula direction.

After use, some talc may remain in the vial. Discard unused portion.

STERITALC 3 grams dosage form

Keep the product upright during use. Avoid contact between the cannula tip and tissue/body fluids. Otherwise the cannula may be blocked. In case of blockage: Shorten the cannula with a scalpel to be able to continue the intervention. Cut perpendicularly to the cannula and ensure that the cutting edge is straight and free of burs.

Step 1: Introduce the cannula into the trocar.

Step 2: Distribute the talc evenly in the pleural cavity. To do this, press the insufflation bulb carefully and at regular intervals. After spraying a few times, change the cannula direction.

After use, some talc may remain in the vial. Discard unused portion

3. DOSAGE FORMS AND STRENGTHS

White or off-white to light gray sterile powder provided in the following strengths:

- Powder, for intrapleural use: STERITALC, 2 grams in a 50 mL single-dose vial
- Powder, for intrapleural use: STERITALC, 4 grams in a 50 mL single-dose vial
- Powder, for intrapleural use: STERITALC, 3 grams in a 10 mL single-dose vial, for use with Novatech SA’s NOVATECH® TALCAIR™

4. CONTRAINDICATIONS

Due to lead content, STERITALC® is contraindicated in pregnant women and can cause fetal harm and potential loss of pregnancy [see Warnings and Precautions (5.3) and Use in Specific Populations (8.1)].

5. WARNINGS AND PRECAUTIONS

5.1 Pneumonitis and Acute Respiratory Distress Syndrome (ARDS)

Acute Pneumonitis and ARDS, including fatal cases, have been reported with intrapleural use of various talc products. Systemic exposure of talc could be affected by the integrity of the visceral pleura and could be increased if talc is administered immediately after mechanical abrasion or biopsy of the pleura. The literature also suggests a possible correlation between talc particle size distribution and risk of toxicity.

There are published reports of two large, prospective trials conducted to evaluate the safety of STERITALC administered intrapleurally. One trial evaluated 558 patients treated with STERITALC 4g by poudrage for MPE. The second trial evaluated 418 patients with recurrent primary spontaneous pneumothorax treated with STERITALC 2 g by poudrage. No cases of ARDS or talc-related lung injury were reported.

5.2 Interference with Future Procedures

Sclerosis of the pleural space may preclude or complicate subsequent ipsilateral surgery and diagnostic procedures. Consider the possible effects of the use of STERITALC on future diagnostic and therapeutic procedures prior to administration.

5.3 Lead Content

Lead is present in STERITALC as an impurity. The main target organ for lead toxicity is the nervous system, but effects of lead exposure also include increased blood pressure, anemia, decreased sperm production, and damage to the kidneys in children and adults. Minimal risk levels of lead have not been derived for humans because clear thresholds for effects have not been identified.

Children are more sensitive to lead toxicity than adults, and no safe blood level has been determined in children. Cognitive and neurobehavioral deficits are observed in children exposed to lead. Exposure of a pregnant woman to lead may cause miscarriage, premature birth, lower birth weights and slow or impaired mental development in the child.

Administration of STERITALC at the highest recommended dose of 10 grams may deliver up to 40 mcg of lead.

5.4 Asbestos Content

Talc products may contain trace amounts of asbestos. Asbestos is a known human carcinogen. Exposure to asbestos may increase the risk of mesotheliomas and other cancers including lung, larynx, and ovarian cancer.

STERITALC is tested for asbestos and asbestiform fibers [see DESCRIPTION (11)].

RECENT MAJOR CHANGES

5.4 Asbestos Content

Talc products may contain trace amounts of asbestos. Asbestos is a known human carcinogen. Exposure to asbestos may increase the risk of mesotheliomas and other cancers including lung, larynx, and ovarian cancer.

STERITALC is tested for asbestos and asbestiform fibers [see DESCRIPTION (11)].

6. ADVERSE REACTIONS

The following clinically significant adverse reactions are described elsewhere in the labeling.

- Pneumonitis and Acute Respiratory Distress Syndrome (ARDS) [see Warnings and Precautions (5.1)]
- Lead Content [see Warnings and Precautions (5.3)]
- Asbestos Content [see Warnings and Precautions (5.4)]

Common adverse reactions observed with intrapleural use of various talc products are fever and pain.

Other adverse reactions include dyspnea, arrhythmia, empyema, pneumonitis and acute respiratory distress syndrome (ARDS).

Procedure related adverse reactions such as bleeding, hemothorax, wound infections, atelectasis and pneumonia may occur.

8. USE IN SPECIFIC POPULATIONS

8.1 Pregnancy

Risk Summary

STERITALC is contraindicated for use in pregnant women because it contains lead, which can cause fetal harm and potential loss of pregnancy [see Warnings and Precautions (5.3)]. There are no human data on the use of STERITALC in pregnant women. In an animal reproduction study, oral administration of talc in pregnant rabbits during organogenesis revealed no evidence of teratogenicity at dose up to approximately 5 times the human dose [see Data].

Data

Animal Data

In an embryo-fetal developmental toxicity study in rabbits, talc was administered to rabbits by oral gavage daily during the period of organogenesis at doses up to 900 mg/kg (approximately 5 times the human dose on a mg/m2 basis). No significant dose-related toxicity was reported except at maternally toxic doses. In multiple animal studies, intrapleurally administered talc was not absorbed systemically.

8.2 Lactation

Risk Summary

There is no information regarding the presence of talc in human milk, the effects on the breastfed infants, or the effects on milk production. STERITALC contains lead, which is known to have adverse effects on health and development in neonates, infants and children [see Warnings and Precautions (5.3)]. Because of the potential for serious adverse reactions in breast-fed infants from lead content in STERITALC, advise lactating women not to breastfeed during treatment with STERITALC and for 5 months after the final dose.

8.3 Females and Males of Reproductive Potential

Contraception

STERITALC contains lead, which can cause fetal harm when administered to a pregnant woman [see Warnings and Precautions (5.3) and Use in Specific Populations (8.1)]. Advise females of reproductive potential to use effective contraception during treatment and for 5 months following the final dose of STERITALC.

Infertility

STERITALC contains lead, which may impair fertility in males of reproductive potential [see Warnings and Precautions (5.3)].

8.4 Pediatric Use

Safety and effectiveness have not been established in pediatric patients. Lead is present in STERITALC as an impurity [see Warnings and Precautions (5.3)].

11. DESCRIPTION

STERITALC (talc) is a sclerosing agent for intrapleural administration. The molecular formula for talc is Mg3Si4O10(OH)2. The molecular weight is 379.3 g/mole. The chemical name of talc is hydrated magnesium silicate.

The talc powder contains ≥ 95% of hydrated magnesium silicate; associated minerals include chlorites (hydrated aluminum and magnesium silicates), magnesite (magnesium carbonate), calcite (calcium carbonate), and dolomite (calcium and magnesium carbonate). The talc elementary sheet is composed of a layer of magnesium-oxygen/hydroxyl octahedra, sandwiched between two layers of silicon-oxygen tetrahedra. Talc is insoluble in water.

STERITALC is tested for asbestos and asbestiform fibers consistent with USP standards for talc-containing products.

STERITALC is supplied as 2 grams, 3 grams, and 4 grams white or off-white to light gray, sterile powder. STERITALC contains particle size-controlled talc, graded to decrease the proportion of smaller particles.

12. CLINICAL PHARMACOLOGY

12.1 Mechanism of Action

Talc instilled into the pleural cavity is thought to result in an inflammatory reaction. This reaction promotes adherence of the visceral and parietal pleura to prevent reaccumulation of pleural air or fluid.

13. NONCLINICAL TOXICOLOGY

13.1 Carcinogenesis, Mutagenesis, Impairment of Fertility

Studies on the carcinogenicity of talc have been performed using non-standard designs which prevent firm conclusions on its carcinogenicity. With single intraperitoneal administration to mice at 20 mg and observation for at least 6 months, or 4 weekly doses administered intraperitoneally at 25 mg/dose to rats with observation for at least 84 weeks, tumor incidence was not increased. In these studies the talc and its asbestos content were not characterized.

Genotoxicity was tested in cultures of rat pleural mesothelial cells (RPMC) for unscheduled DNA synthesis (UDS) and sister chromatid exchanges (SCEs). None of the talc samples induced enhancement of UDS or SCEs in treated cultures.

No information is available on impairment of fertility in animals by talc.

14. CLINICAL STUDIES

14.1 Malignant Pleural Effusion

The data demonstrating safety and efficacy of talc in the treatment of malignant pleural effusions are derived from the published medical literature. In these studies, greater than 1000 patients with malignant pleural effusions have been reported (with varying degrees of detail and durations of response) to have had successful pleurodesis with talc, administered either by poudrage or as a slurry via chest tube. There are published efficacy data for more than 200 patients treated with STERITALC for malignant pleural effusion, with a success rate of approximately 89% (range 73-91%).

14.2 Pneumothorax

The data demonstrating safety and efficacy of talc in the treatment of pneumothorax are derived from the published medical literature. There are published efficacy data for more than 500 patients treated with STERITALC for pneumothorax, some in conjunction with surgical procedures, with successful pleurodesis rates of 97-100%.

16. HOW SUPPLIED/STORAGE AND HANDLING

STERITALC, white or off-white to light gray, sterile powder is supplied as

- two grams of talc powder in a single-dose 50 mL Type III glass vial, closed with a stopper, and crimped with an aluminum cap; with 4 vials packaged in one carton.
- NDC 62327-222-02 (vial)

NDC 62327-222-42 (carton)

four grams of talc powder in a single-dose 50 mL Type III glass vial, closed with a stopper, and crimped with an aluminum cap; with 4 vials packaged in one carton.

NDC 62327-444-04 (vial)
NDC 62327-444-44 (carton)

- three grams of talc powder in a single-dose 10 mL Type I brown glass vial, closed with a stopper, and crimped with an aluminum cap; with 4 vials packaged in one carton.

NDC 62327-333-03 (vial)
NDC 62327-333-43 (carton)

Store at 20°C - 25°C (68°F - 77°F); excursions permitted between 15°C - 30°C (59°F - 86°F) [see USP Controlled Room Temperature]. Protect against sunlight.

17. PATIENT COUNSELLING INFORMATION

- Advise patients to notify their healthcare provider if new or worsening pulmonary symptoms develop [see Warnings and Precautions (5.1)].

- Inform patients that the lead content in STERITALC can be harmful to a developing fetus. Advise females of reproductive potential to use effective contraception during treatment and for 5 months after the last dose of STERITALC [see Warnings and Precautions (5.3) and Use in Specific Populations (8.3)].

Manufactured for: Novatech SA

Z.I. Athélia III - 1058, Voie Antiope

13705 La Ciotat CEDEX

France

By: bess pro gmbh

Gustav-Krone-Strasse 7

14167 Berlin

Germany

NO128-03

Steritalc final carton label 4g N444